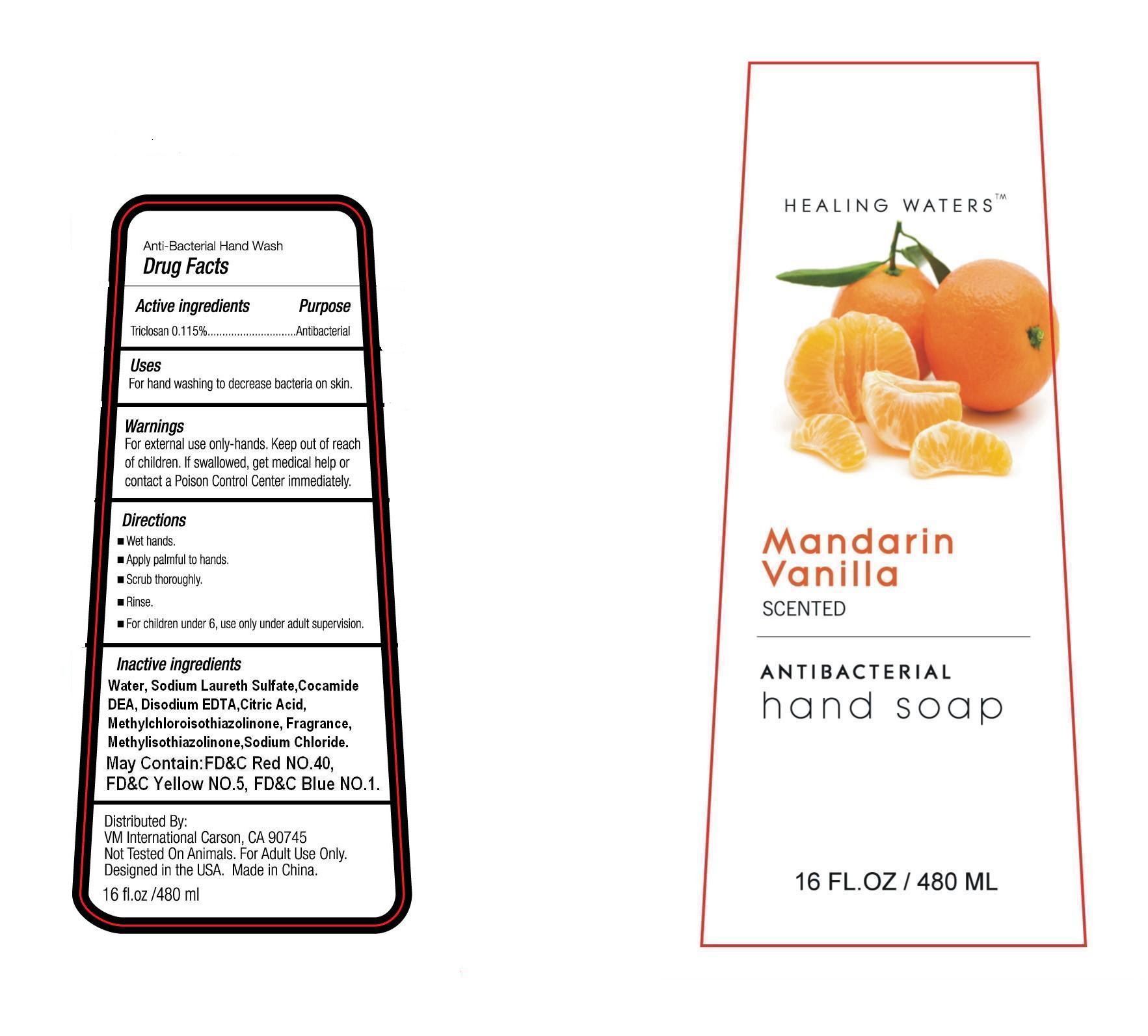 DRUG LABEL: Healing Waters Mandarin Vanilla Antibacterial Hand Soap
NDC: 50593-003 | Form: LIQUID
Manufacturer: Taizhou Xinzhixuan Daily-Use Co., Ltd.
Category: otc | Type: HUMAN OTC DRUG LABEL
Date: 20100505

ACTIVE INGREDIENTS: TRICLOSAN 0.115 g/100 g
INACTIVE INGREDIENTS: WATER 80.97499 g/100 g; SODIUM LAURETH SULFATE 12.0 g/100 g; COCAMIDE DIETHANOLAMINE 5.0 g/100 g; EDETATE DISODIUM 0.08 g/100 g; ANHYDROUS CITRIC ACID 0.15 g/100 g; METHYLCHLOROISOTHIAZOLINONE 0.04 g/100 g; METHYLISOTHIAZOLINONE 0.04 g/100 g; SODIUM CHLORIDE 1.2 g/100 g; FD&C RED NO. 40 0.000004 g/100 g; FD&C YELLOW NO. 5 0.000004 g/100 g; FD&C BLUE NO. 1 0.000002 g/100 g; VANILLA 0.2 g/100 g

Drug Fact

Active Ingredients Purpose
Triclosan 0.115% Antibacterial

Uses
For hand washing to decrease bacteria on skin

Warnings
For external use only-hands. Keep out of reach of children. If swallowed, get medical help or contact a Poison Control Center immediately

Directions

- Wet hands
- Apply palmful to hands
- Scrub thoroughly
- Rinse
- For children under 6,use only under adult supervision.

Inactive Ingredients

water(Aqua), Sodium Laureth Sulfate, Cocamide DEA, Disodium EDTA, Citric Acid, Methylchloroisothiazolinone, Fragrance, Methylisothiazolinone, Sodium Chloride. May contain: FD and C Red No. 40, FD and C Yellow No. 5, FD and C Blue No. 1

PACKAGE LABEL

lab